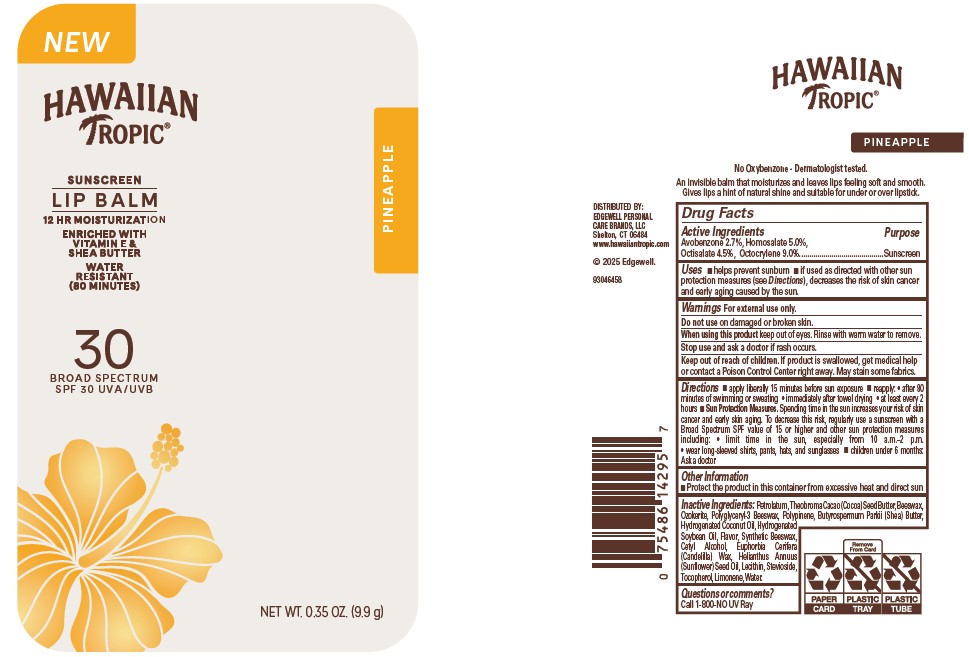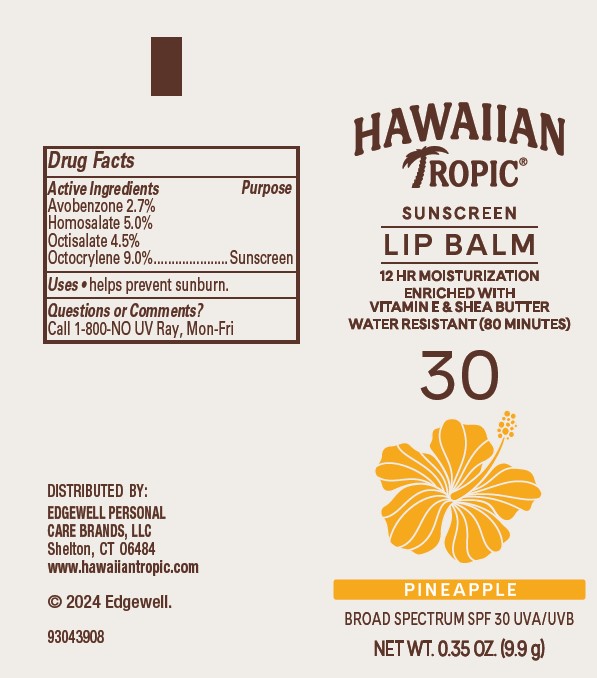 DRUG LABEL: HAWAIIAN TROPIC
NDC: 63354-804 | Form: GEL
Manufacturer: Edgewell Personal Care Brands LLC
Category: otc | Type: HUMAN OTC DRUG LABEL
Date: 20260105

ACTIVE INGREDIENTS: OCTISALATE 4.5 g/100 g; HOMOSALATE 5 g/100 g; AVOBENZONE 2.7 g/100 g; OCTOCRYLENE 9 g/100 g
INACTIVE INGREDIENTS: SYNTHETIC BEESWAX; CANDELILLA WAX; STEVIOSIDE; COCOA BUTTER; HYDROGENATED COCONUT OIL; SUNFLOWER OIL; SHEA BUTTER; HYDROGENATED SOYBEAN OIL; YELLOW WAX; TOCOPHEROL; CETYL ALCOHOL; PETROLATUM; POLYGLYCERYL-3 BEESWAX; WATER; CERESIN

Active Ingredients

Avobenzone 2.7%, Homosalate 5.0%, Octisalate 4.5%, Octocrylene 9.0%.

Purpose

Sunscreen

Uses

•helps prevent sunburn • if used as directed with other sun protection measures (see Directions), decreases the risk of skin cancer and early aging caused by the sun.

Warnings

For external use only.

May stain some fabrics.

Do not use

on damaged or broken skin.

When using this product

keep out of eyes. Rinse with warm water to remove.

Stop use and ask a doctor

if rash occurs.

Keep out of reach of children.

If product is swallowed, get medical help or contact a Poison Control Center right away.

Directions

• apply liberally 15 minutes before sun exposure • reapply: • after 80 minutes of swimming or sweating • immediately after towel drying • at least every 2 hours • Sun Protection Measures. Spending time in the sun increases your risk of skin cancer and early skin aging. To decrease this risk, regularly use a sunscreen with a Broad Spectrum SPF value of 15 or higher and other sun protection measures including: • limit time in the sun, especially from 10 a.m.–2 p.m. • wear long-sleeved shirts, pants, hats, and sunglasses • children under 6 months: Ask a doctor

Inactive Ingredients:

Petrolatum, Theobroma Cacao (Cocoa) Seed Butter, Beeswax, Ozokerite, Polyglyceryl-3 Beeswax, Polydipentene, Butyrospermum Parkii (Shea) Butter, Hydrogenated Coconut Oil, Hydrogenated Soybean Oil, Flavor, Synthetic Beeswax, Cetyl Alcohol, Euphorbia Cerifera (Candelilla) Wax, Helianthus Annuus (Sunflower) Seed Oil, Lecithin, Stevioside, Tocopherol, Water.

Other Information

•Protect the product in this container from excessive heat and direct sun

Questions or comments?

Call 1-800-NO UV Ray

PRINCIPAL DISPLAY PANEL

NEW

HAWAIIAN

TROPIC

SUNSCREEN

LIP BALM

12 HR MOISTURIZATION

ENRICHED WITH

VITAMIN E &

SHEA BUTTER

WATER

RESISTANT

(80 MINUTES)

30

BROAD SPECTRUM

SPF 30 UVA / UVB

NET WT. 0.35 OZ. (9.9 g)

HAWAIIAN

TROPIC

SUNSCREEN

LIP BALM

12 HR MOISTURIZATION

ENRICHED WITH

VITAMIN E &

SHEA BUTTER

WATER RESISTANT (80 MINUTES)

30

PINEAPPLE

BROAD SPECTRUM SPF 30 UVA / UVB

NET WT. 0.35 OZ. (9.9 g)